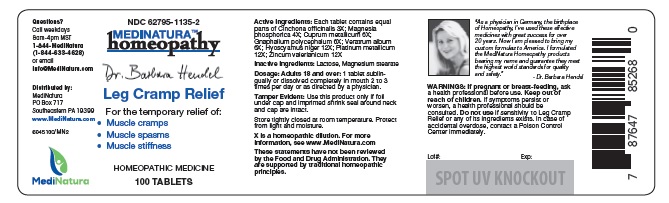 DRUG LABEL: Hendel Leg Cramp
NDC: 62795-1135 | Form: TABLET
Manufacturer: MediNatura Inc
Category: homeopathic | Type: HUMAN OTC DRUG LABEL
Date: 20190610

ACTIVE INGREDIENTS: CINCHONA OFFICINALIS BARK 3 [hp_X]/1 1; MAGNESIUM PHOSPHATE, DIBASIC TRIHYDRATE 4 [hp_X]/1 1; COPPER 6 [hp_X]/1 1; PSEUDOGNAPHALIUM OBTUSIFOLIUM 6 [hp_X]/1 1; VERATRUM ALBUM ROOT 6 [hp_X]/1 1; HYOSCYAMUS NIGER 12 [hp_X]/1 1; PLATINUM 12 [hp_X]/1 1; ZINC VALERATE DIHYDRATE 12 [hp_X]/1 1
INACTIVE INGREDIENTS: LACTOSE, UNSPECIFIED FORM; Magnesium stearate

Hendel Leg Cramp

WARNINGS

If pregnant or breast-feeding, ask a health professional before use. Keep out of reach of children. If symptoms persist or worsen, a health professional should be consulted. Do not use if sensitivity to Leg Cramp Relief

KEEP OUT OF REACH OF CHILDREN

INDICATIONS

Leg Cramp Relief

INGREDIENTS

Each tablet contains equal parts of Cinchona officinalis 3X; Magnesia phosphorica 4X; Cuprum metallicum 6X; Gnaphalium polycephalum 6X; Veratrum album 6X; Hyoscyamus niger 12X; Platinum metallicum 12X; Zincum valerianicum 12X.

INACTIVE INGREDIENT

Lactose, Magnesium stearate

USES

For the temporary relief of:
• Muscle Cramp
• Muscle Spasm
• Muscle Stiffness

DIRECTIONS

Adults 18 and over: 1 tablet sublingually or dissolved completely in mouth 2 to 3 times per day or as directed by a physician